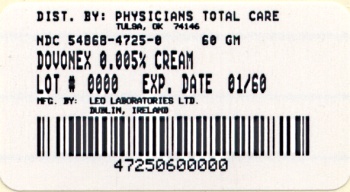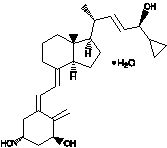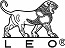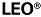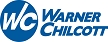 DRUG LABEL: Dovonex
NDC: 54868-4725 | Form: CREAM
Manufacturer: Physicians Total Care, Inc.
Category: prescription | Type: HUMAN PRESCRIPTION DRUG LABEL
Date: 20091125

ACTIVE INGREDIENTS: CALCIPOTRIENE 50 ug/1 g
INACTIVE INGREDIENTS: CETOSTEARYL ALCOHOL; CETETH-20; DICHLOROBENZYL ALCOHOL; SODIUM PHOSPHATE, DIBASIC; EDETATE DISODIUM; GLYCERIN; MINERAL OIL; PETROLATUM; WATER

Dovonex®
(calcipotriene cream)
Cream, 0.005%

Rx only

FOR TOPICAL DERMATOLOGIC USE ONLY.
Not for Ophthalmic, Oral or Intravaginal Use.

DESCRIPTION

Dovonex® (calcipotriene cream) Cream, 0.005% contains calcipotriene monohydrate, a synthetic vitamin D3 derivative, for topical dermatological use.

Chemically, calcipotriene monohydrate is (5Z,7E,22E,24S)-24-cyclopropyl-9,10-secochola-5,7,10(19),22-tetraene-1α,3β,24-triol monohydrate, with the empirical formula C27H40O3•H2O, a molecular weight of 430.6, and the following structural formula:

Calcipotriene monohydrate is a white or off-white crystalline substance. Dovonex® Cream contains calcipotriene monohydrate equivalent to 50 μg/g anhydrous calcipotriene in a cream base of cetearyl alcohol, ceteth-20, diazolidinyl urea, dichlorobenzyl alcohol, dibasic sodium phosphate, edetate disodium, glycerin, mineral oil, petrolatum, and water.

CLINICAL PHARMACOLOGY

In humans, the natural supply of vitamin D depends mainly on exposure to the ultraviolet rays of the sun for conversion of 7-dehydrocholesterol to vitamin D3 (cholecalciferol) in the skin. Calcipotriene is a synthetic analog of vitamin D3.

Clinical studies with radiolabelled calcipotriene ointment indicate that approximately 6% (± 3%, SD) of the applied dose of calcipotriene is absorbed systemically when the ointment is applied topically to psoriasis plaques, or 5% (± 2.6%, SD) when applied to normal skin, and much of the absorbed active is converted to inactive metabolites within 24 hours of application. Systemic absorption of the cream has not been studied.

Vitamin D and its metabolites are transported in the blood, bound to specific plasma proteins. The active form of the vitamin, 1,25-dihydroxy vitamin D3 (calcitriol), is known to be recycled via the liver and excreted in the bile. Calcipotriene metabolism following systemic uptake is rapid, and occurs via a similar pathway to the natural hormone.

CLINICAL STUDIES

Adequate and well-controlled trials of patients treated with Dovonex® Cream have demonstrated improvement usually beginning after 2 weeks of therapy. This improvement continued with approximately 50% of patients showing at least marked improvement in the signs and symptoms of psoriasis after 8 weeks of therapy, but only approximately 4% showed complete clearing.

INDICATIONS AND USAGE

Dovonex® (calcipotriene cream) Cream, 0.005%, is indicated for the treatment of plaque psoriasis. The safety and effectiveness of topical calcipotriene in dermatoses other than psoriasis have not been established.

CONTRAINDICATIONS

Dovonex® Cream is contraindicated in those patients with a history of hypersensitivity to any of the components of the preparation. It should not be used by patients with demonstrated hypercalcemia or evidence of vitamin D toxicity. Dovonex® Cream should not be used on the face.

PRECAUTIONS

General

Use of Dovonex® Cream may cause transient irritation of both lesions and surrounding uninvolved skin. If irritation develops, Dovonex® Cream should be discontinued.

For external use only. Keep out of the reach of children. Always wash hands thoroughly after use.

Reversible elevation of serum calcium has occurred with use of topical calcipotriene. If elevation in serum calcium outside the normal range should occur, discontinue treatment until normal calcium levels are restored.

Information for Patients

Patients using Dovonex® Cream should receive the following information and instructions:

1. This medication is to be used only as directed by the physician. It is for external use only. Avoid contact with the face or eyes. As with any topical medication, patients should wash their hands after application.
2. This medication should not be used for any disorder other than that for which it was prescribed.
3. Patients should report to their physician any signs of adverse reactions.
4. Patients that apply Dovonex® to exposed portions of the body should avoid excessive exposure to either natural or artificial sunlight (including tanning booths, sun lamps, etc.).

Carcinogenesis, Mutagenesis, Impairment of Fertility

When calcipotriene was applied topically to mice for up to 24 months at dosages of 3, 10 and 30 µg/kg/day (corresponding to 9, 30 and 90 µg/m^2/day), no significant changes in tumor incidence were observed when compared to control. In a study in which albino hairless mice were exposed to both UVR and topically applied calcipotriene, a reduction in the time required for UVR to induce the formation of skin tumors was observed (statistically significant in males only), suggesting that calcipotriene may enhance the effect of UVR to induce skin tumors. Patients that apply Dovonex® to exposed portions of the body should avoid excessive exposure to either natural or artificial sunlight (including tanning booths, sun lamps, etc.). Physicians may wish to limit or avoid use of phototherapy in patients that use Dovonex®.

Calcipotriene did not elicit any mutagenic effects in an Ames mutagenicity assay, a mouse lymphoma TK locus assay, a human lymphocyte chromosome aberration assay, or in a micronucleus assay conducted in mice.

Studies in rats at doses up to 54 μg/kg/day (324 μg/m^2/day) of calcipotriene indicated no impairment of fertility or general reproductive performance.

Pregnancy

Teratogenic Effects: Pregnancy Category C

Studies of teratogenicity were done by the oral route where bioavailability is expected to be approximately 40-60% of the administered dose. Increased rabbit maternal and fetal toxicity was noted at 12 μg/kg/day (132 μg/m^2/day). Rabbits administered 36 μg/kg/day (396 μg/m^2/day) resulted in fetuses with a significant increase in the incidences of pubic bones, forelimb phalanges, and incomplete bone ossification. In a rat study, oral doses of 54 μg/kg/day (318 μg/m^2/day) resulted in a significantly higher incidence of skeletal abnormalities consisting primarily of enlarged fontanelles and extra ribs. The enlarged fontanelles are most likely due to calcipotriene's effect upon calcium metabolism. The maternal and fetal calculated no-effect exposures in the rat (43.2 μg/m^2/day) and rabbit (17.6 μg/m^2/day) studies are approximately equal to the expected human systemic exposure level (18.5 μg/m^2/day) from dermal application. There are no adequate and well-controlled studies in pregnant women. Therefore, Dovonex® Cream should be used during pregnancy only if the potential benefit justifies the potential risk to the fetus.

Nursing Mothers

There is evidence that maternal 1,25-dihydroxy vitamin D3 (calcitriol) may enter the fetal circulation, but it is not known whether it is excreted in human milk. The systemic disposition of calcipotriene is expected to be similar to that of the naturally occurring vitamin. Because many drugs are excreted in human milk, caution should be exercised when Dovonex® Cream is administered to a nursing woman.

Pediatric Use

Safety and effectiveness of Dovonex® Cream in pediatric patients have not been established. Because of a higher ratio of skin surface area to body mass, pediatric patients are at greater risk than adults of systemic adverse effects when they are treated with topical medication.

Geriatric Use

Of the total number of patients in clinical studies of calcipotriene cream, approximately 15% were 65 or older, while approximately 3% were 75 and over. There were no significant differences in adverse events for subjects over 65 years compared to those under 65 years of age. However, the greater sensitivity of older individuals cannot be ruled out.

ADVERSE REACTIONS

In controlled clinical trials, the most frequent adverse experiences reported for Dovonex® (calcipotriene cream) Cream, 0.005% were cases of skin irritation, which occurred in approximately 10-15% of patients. Rash, pruritus, dermatitis and worsening of psoriasis were reported in 1 to 10% of patients.

OVERDOSAGE

Topically applied calcipotriene can be absorbed in sufficient amounts to produce systemic effects. Elevated serum calcium has been observed with excessive use of topical calcipotriene. If elevation in serum calcium should occur, discontinue treatment until normal calcium levels are restored. (See PRECAUTIONS.)

DOSAGE AND ADMINISTRATION

Apply a thin layer of Dovonex® Cream to the affected skin twice daily and rub in gently and completely. The safety and efficacy of Dovonex® Cream have been demonstrated in patients treated for eight weeks.

HOW SUPPLIED

Dovonex® (calcipotriene cream) Cream, 0.005% is available in:

60 gram aluminum tubes NDC 54868-4725-0

STORAGE

Store at controlled room temperature 15° C - 25° C (59° F - 77° F). Do not freeze.

Manufactured by LEO Laboratories Ltd.
Dublin, Ireland

Marketed by:
Warner Chilcott (US), LLC
Rockaway, NJ 07866 USA
1-800-521-8813

U.S. Patent No. RE39,706 E

3020G062

3020G012 Revised February 2008

Relabeling of "Additional" barcode label by:
Physicians Total Care, Inc.
Tulsa, OK 74146

PRINCIPAL DISPLAY PANEL

Dovonex®
(calcipotriene cream),
0.005% Cream

Rx only

WARNING: Keep Out of Reach of Children

Each gram contains 0.05 mg of
calcipotriene in a cream base of
cetearyl alcohol, ceteth-20,
diazolidinyl urea, dichlorobenzyl
alcohol, dibasic sodium phosphate,
edetate disodium, glycerin, mineral
oil, petrolatum, and water.

For Topical Dermatologic Use Only.
Not for Ophthalmic, Oral, or
Intravaginal Use.

Usual Dosage: Apply twice daily,
or as directed by physician. See
insert for complete information.
Read all Panels.

NET WT. 60 g

Store at controlled room temperature
15° C - 25° C (59° F - 77° F).
Do not freeze
Lot no. and expiration date on carton end and crimp of tube.